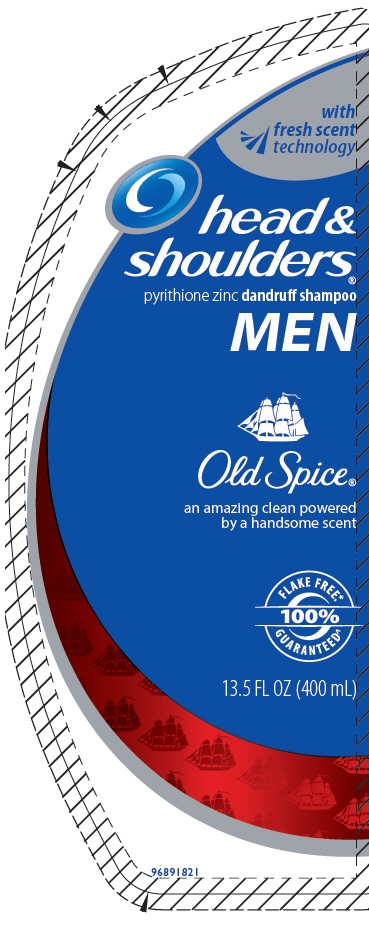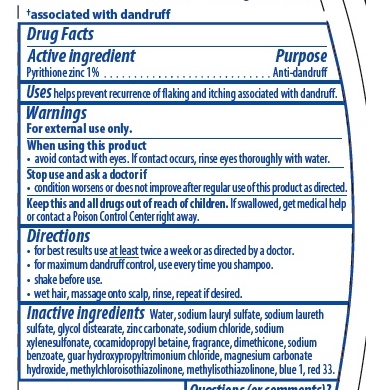 DRUG LABEL: HEAD AND  SHOULDER
NDC: 51769-427 | Form: LOTION/SHAMPOO
Manufacturer: All Natural Dynamics
Category: otc | Type: HUMAN OTC DRUG LABEL
Date: 20220510

ACTIVE INGREDIENTS: PYRITHIONE ZINC 0.01 mg/1 mg
INACTIVE INGREDIENTS: WATER; ZINC CARBONATE; SODIUM CHLORIDE; SODIUM XYLENESULFONATE; COCAMIDOPROPYL BETAINE; DIMETHICONE; SODIUM BENZOATE; MAGNESIUM CARBONATE HYDROXIDE; METHYLISOTHIAZOLINONE; FD&C BLUE NO. 1; D&C RED NO. 33; SODIUM LAURYL SULFATE; SODIUM LAURETH-3 SULFATE; METHYLCHLOROISOTHIAZOLINONE; GLYCOL DISTEARATE

ACTIVE INGREDIENT

DRUGS FACTS

ACTIVE INGREDIENTS

Pyrithione zinc 1%

PURPOSE

Anti-dandruff

USES

Help prevent recurrence of flaking and itching associated with dan druff

WARNINGS

FOR EXTERNAL USE ONLY

WHEN USING THIS PRODUCT

Avoid contact with eyes. if contact occurs, rinse eyes thoroughly with water.

STOP USE AND ASK A DOCTOR IF

condition worsens or does not improve after regular use of this procuct as directed.

KEEP OUT OF REACH OF CHILDREN

KEEP THIS AND ALL DRUGS OUT OF REACH OF CHILDREN. If swallowed, get medical help or contact a poison control center rigth away.

DIRECTIONS

- for best results use at least twice a week or as directed by doctor.
- for maximun dandruff control, use every time you shampoo
- shake bedore use
- wet hair, message onto scalp, rinse, repeat if desired.

INACTIVE INGREDIENT

WATER, SODIUM LAURYL SULFATE, SODIUM LAURETH SULDATE, GLYCOL DISTEARATE , ZINC CARBONATE, SODIUM CHLORIDE, SODIUM XYLENESULFONATE, COCAMIDOPROPYL BETAINE, FRAGANCE, DIMETHICONE, SODIUM BENZOATE, GUAR HYDROXYPROPYLTRIMONIUM CHLORIDE, MAGNESIUM CARBONATE HYDROXIDE, METHYLCHLOROISOTHIAZOLINONE, METHYLISOTHIAZOLINONE, BLUE 1, RED 33

INDICATIONS AND USAGE

HELP PREVENT RECURRENCE OF FLAKING AND ITCHING ASSOCIATED WITH DANDRUFF